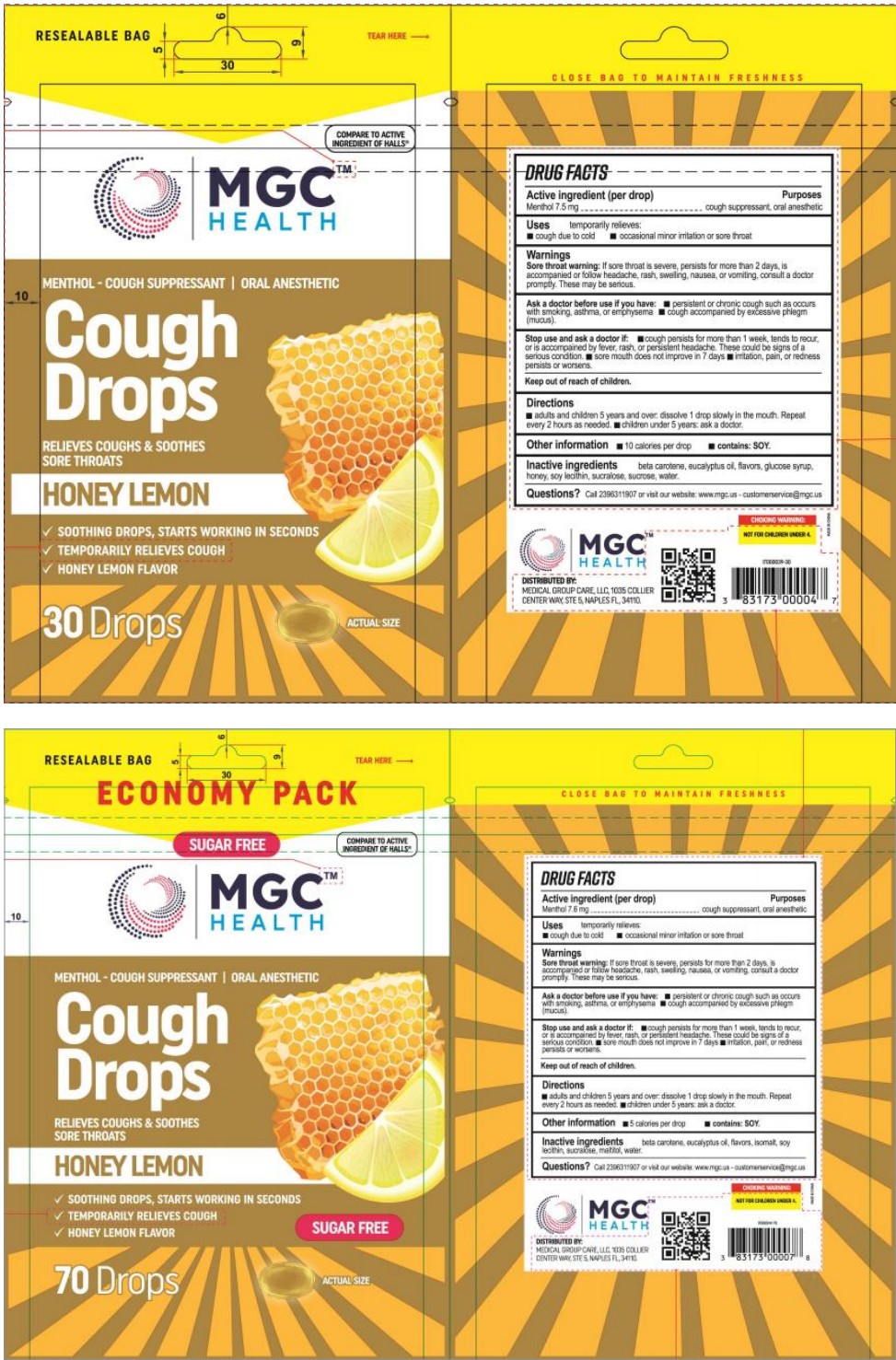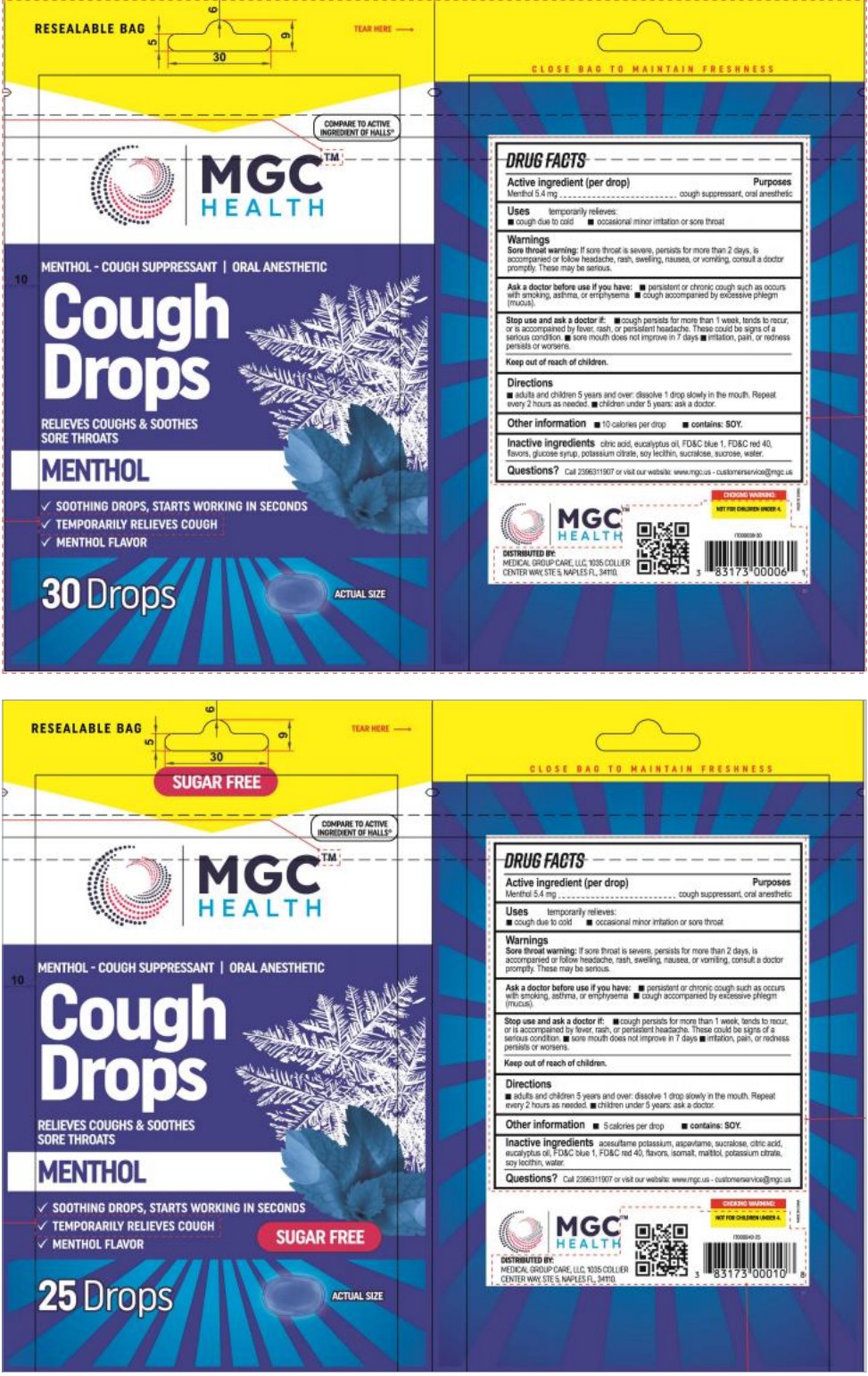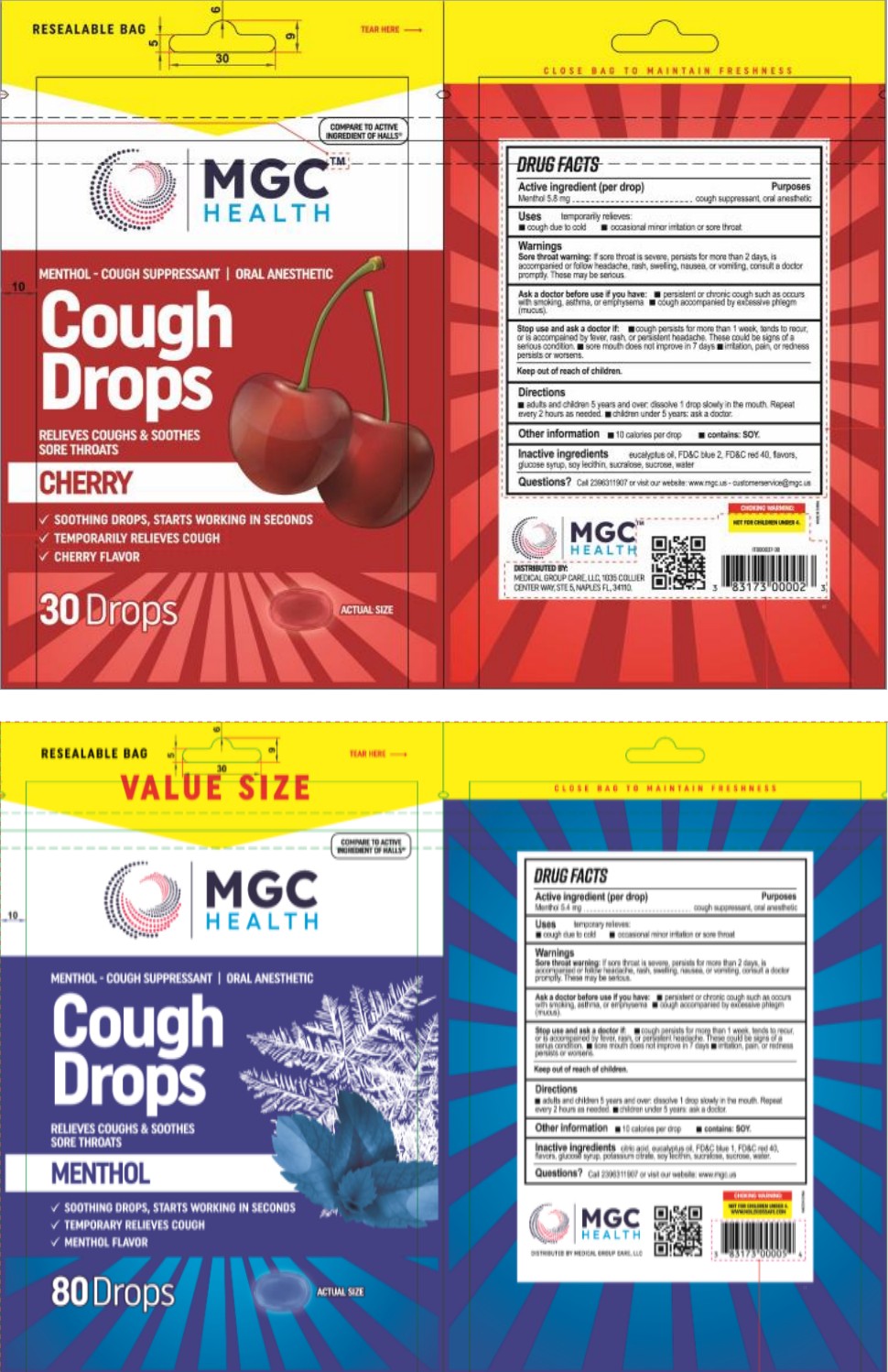 DRUG LABEL: Cough Drops
NDC: 83698-001 | Form: GRANULE
Manufacturer: Xiamen Kang Zhongyuan Biotechnology Co., Ltd.
Category: otc | Type: HUMAN OTC DRUG LABEL
Date: 20230913

ACTIVE INGREDIENTS: MENTHOL 0.18 g/100 1
INACTIVE INGREDIENTS: WATER; CITRIC ACID MONOHYDRATE; CORN SYRUP; POTASSIUM CITRATE; LECITHIN, SOYBEAN; SUCRALOSE; SUCROSE; EUCALYPTUS OIL; FD&C BLUE NO. 1; FD&C RED NO. 40

Active Ingredient

Menthol 0.18%

Purpose

cough suppressant,oral anesthetic

Use

Cough due to cold

Occasional minor imtation or sore throat

Warnings

Sore throat warning: If sore throat is severe,persists for more than 2 days,is accompanied or follow headache,rash,swelling,nausea,or vomiting,consult a doctor promptly. These may be serious.

Do not use

persistent or chronic cough such as occurs cough accompanied by excessive phlegm with smoking, asthma, or emphysema (mucus).

Stop Use

Stop use and ask a doctor if:
1,cough persists for more than 1 week,tends to recur,
or is accompained by fever,rash,or persistent headache.These could be signs of a serius condition.

2, sore mouth does not improve in 7 days

3,irritation, pain, or redness persists or worsens.

Keep Oot Of Reach Of Children

Please do not place this product in an area accessible to unconscious people.

In case of accidental ingestion, seek medical help right away.

Directions

adults and children 5 years and over: dissolve 1 drop slowly in the mouth. Repeat every 2 hours as needed.muchildren under 5 years:ask a doctor.

Other information

1,10calories per drop

2,contains ：soy

Inactive ingredients

citric acid,eucalyptus oil,FD&C blue 1,FD&C red 40, flavors, glucose syrup, potassium citrate,soy lecithin,sucralose,sucrose,water.

Questions

Call2396311907 or visit our website :www.mgc.us